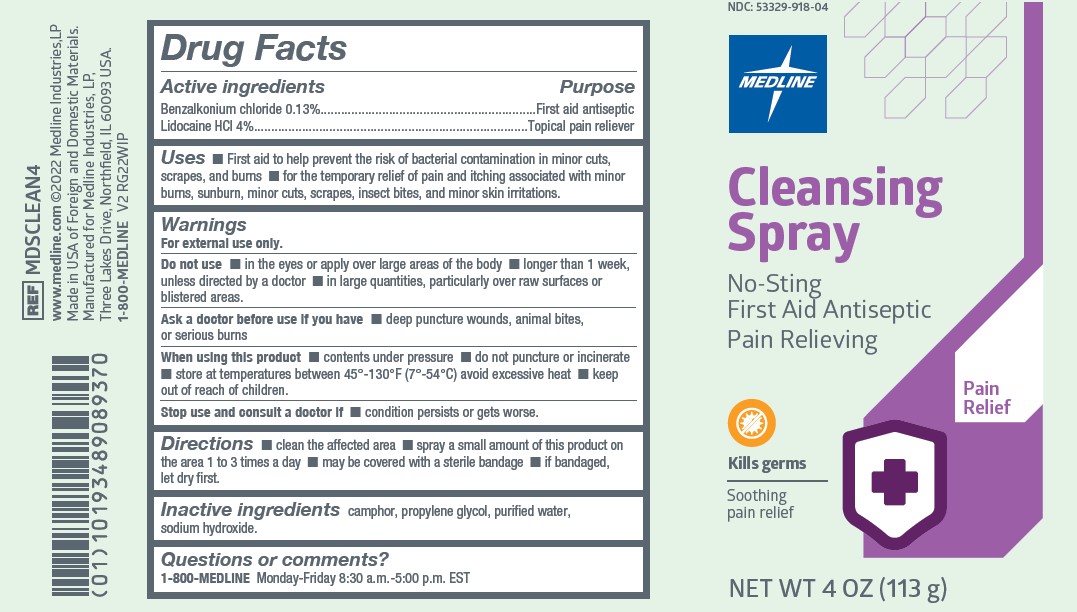 DRUG LABEL: Medline
NDC: 53329-918 | Form: SPRAY
Manufacturer: Medline Industries, LP
Category: otc | Type: HUMAN OTC DRUG LABEL
Date: 20251016

ACTIVE INGREDIENTS: BENZALKONIUM CHLORIDE 0.13 g/100 g; LIDOCAINE HYDROCHLORIDE 4 g/100 g
INACTIVE INGREDIENTS: WATER; PROPYLENE GLYCOL; SODIUM HYDROXIDE; CAMPHOR (SYNTHETIC)

918 Medline Cleansing Spray

Active ingredients

Benzalkonium chloride 0.13% w/w

Lidocaine HCl 4% w/w

Purpose

First aid antiseptic, Topical pain reliever

Uses

- first aid to help prevent the risk of bacterial contamination in minor cuts, scrapes, and burns
- for the temporary relief of pain and itching associated with minor burns, sunburn, minor cuts, scrapes, insect bites, and minor skin irritations

Warnings

For external use only.

Do not use

- in the eyes or apply over large areas of the body
- longer than 1 week, unless directed by a doctor
- in large quantities, particularly over raw surfaces or blistered areas

Ask a doctor before use if you have

- deep puncture wounds, animal bites, or serious burns

When using this product

- contents under pressure
- do not puncture or incinerate
- store at temperatures between 45°-130°F (7°-54°C), avoid excessive heat

Stop use and consult a doctor if

- condition persists or gets worse

Keep out of reach of children.

If accidentally ingested, get medical help or contact a Poison Control Center right away.

Directions

- clean the affected are
- spray a small amount of this product on the area 1 to 3 times a day
- may be covered with a sterile bandage
- if bandaged, let dry first

Inactive ingredients

camphor, propylene glycol, purified water, sodium hydroxide

Questions or comments?

1-800-MEDLINE Monday-Friday 8:30 a.m.-5:00 p.m. EST

Manufacturing Information

Manufactured for: Medline Industries, Inc.

Three Lakes Drive, Northfield, IL 60093 USA

Made in USA of foreign and domestic materials

www.medline.com

1-800-MEDLINE

REF: MDSCLEAN4

V2 RG22WIP